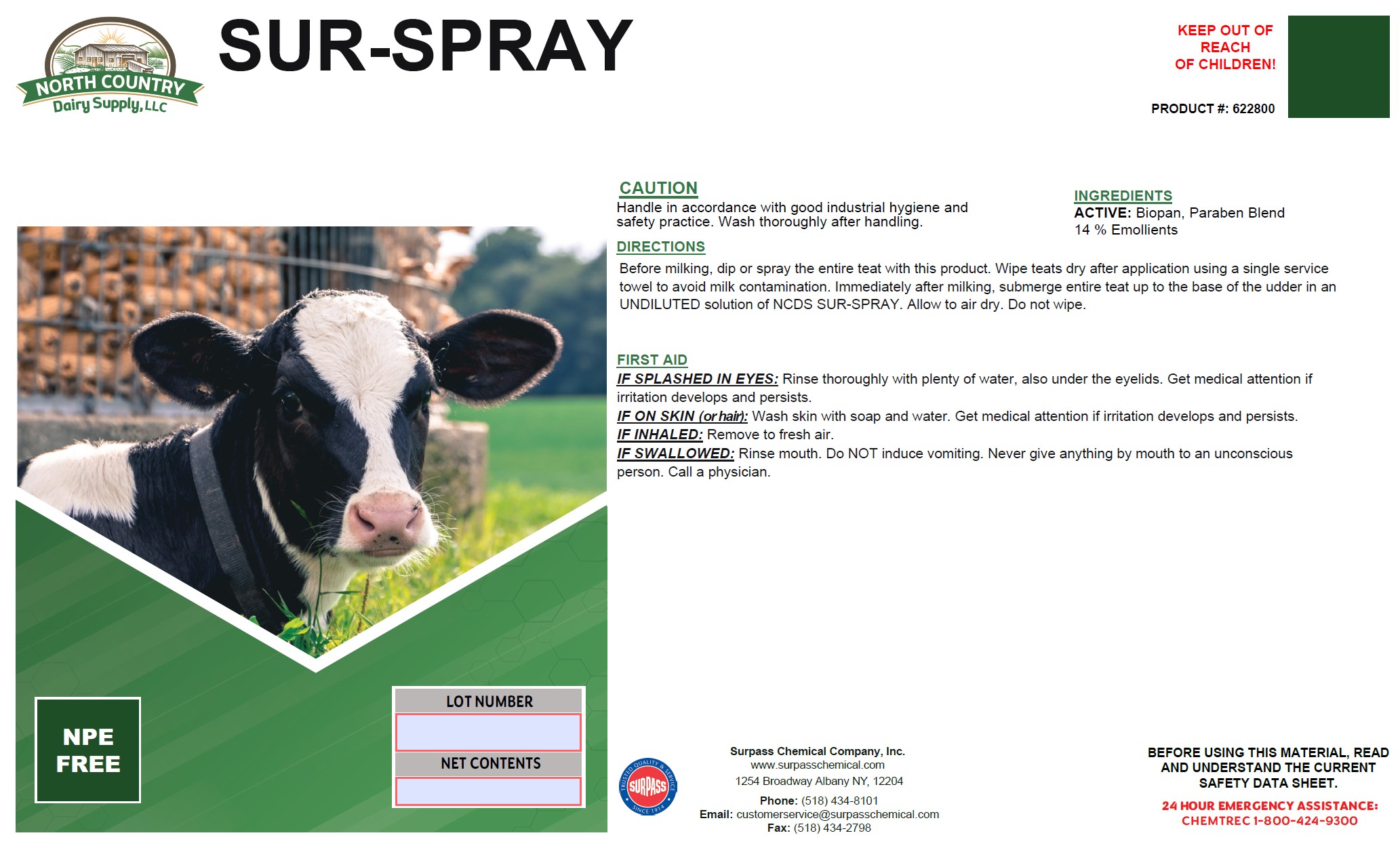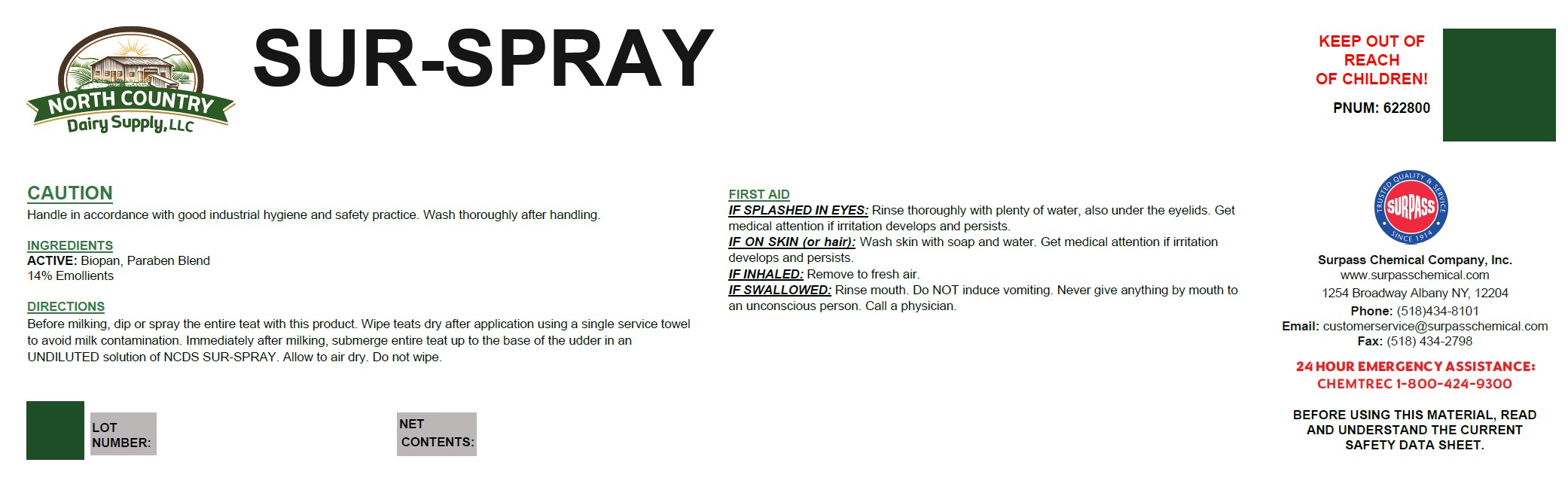 DRUG LABEL: SURSPRAY
NDC: 86067-0130 | Form: SOLUTION
Manufacturer: Surpass Chemical Company, Inc.
Category: animal | Type: OTC ANIMAL DRUG LABEL
Date: 20241209

ACTIVE INGREDIENTS: PROPYLPARABEN 0.001 kg/1 kg; METHYLPARABEN 0.001 kg/1 kg; PROPANEDIOL 0.002 kg/1 kg
INACTIVE INGREDIENTS: WATER 0.82686 kg/1 kg; C9-11 PARETH-3 0.01 kg/1 kg; LANOLIN 0.0889 kg/1 kg; PROPYLENE GLYCOL 0.01 kg/1 kg; GLYCERIN 0.05 kg/1 kg; FD&C BLUE NO. 1 0.0002 kg/1 kg; ANHYDROUS CITRIC ACID 0.00004 kg/1 kg; 2-PROPANOL, 1,1'-OXYBIS(3-(1-NAPHTHALENYLOXY)- 0.01 kg/1 kg

SUR SPRAY

DESCRIPTION

SUR-SPRAY PRODUCT #: 622800

DIRECTIONS:

Before milking, dip or spray the entire teat with this product. Wipe teats dry after application using a single service
towel to avoid milk contamination. Immediately after milking, submerge entire teat up to the base of the udder in an
UNDILUTED solution of NCDS SUR-SPRAY. Allow to air dry. Do not wipe.

ACTIVE INGREDIENT

INGREDIENTS:
ACTIVE: Biopan, Paraben Blend

14% Emolients

OTHER SAFETY INFORMATION

FIRST AID:
IF SPLASHED IN EYES: Rinse thoroughly with plenty of water, also under the eyelids. Get medical attention if irritation develops and persists.
IN CASE OF CONTACT: Wash skin with soap and water. Get medical attention if irritation develops and persists.
IF INHALED: Remove to fresh air.
IF SWALLOWED: Rinse mouth. Do NOT induce vomiting. Never give anything by mouth to an unconscious person. Call a physician.

USER SAFETY WARNINGS

BEFORE USING THIS MATERIAL, READ AND
UNDERSTAND THE CURRENT SAFETY DATA SHEET.

Surpass Chemical Company, Inc. Phone: (518) 434-8101 24 HOUR EMERGENCY ASSISTANCE:
www.surpasschemical.com Fax: (518) 434-2798 CHEMTREC 1-800-424-9300
1254 Broadway Albany NY, 12204 Email: customerservice@surpasschemical.com

KEEP OUT OF REACH OF CHILDREN!